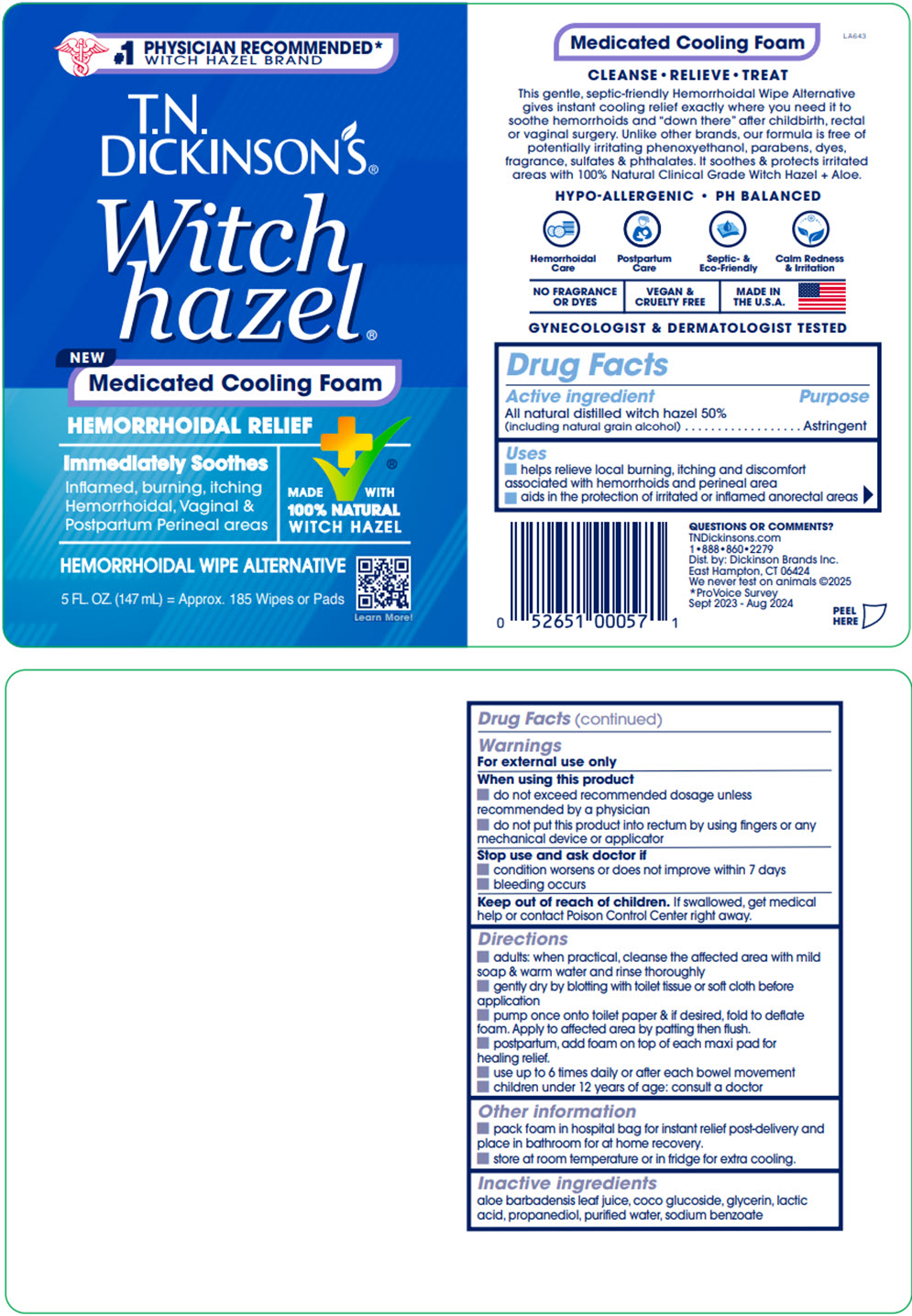 DRUG LABEL: TN Dickinsons Medicated Cooling Foam Hemorrhoidal Relief
NDC: 52651-057 | Form: LIQUID
Manufacturer: Dickinson Brands Inc.
Category: otc | Type: HUMAN OTC DRUG LABEL
Date: 20250627

ACTIVE INGREDIENTS: WITCH HAZEL 0.4 g/1 mL
INACTIVE INGREDIENTS: WATER; GLYCERIN; PROPANEDIOL; SODIUM BENZOATE; ALOE VERA LEAF; LACTIC ACID, UNSPECIFIED FORM; COCO-GLUCOSIDE

T.N. Dickinson's® Medicated Cooling Foam Hemorrhoidal Relief

Drug Facts

Active ingredient

All natural distilled witch hazel 50% (including natural grain alcohol)

Purpose

Astringent

Uses

- helps relieve local burning, itching and discomfort associated with hemorrhoids and perineal area
- aids in the protection of irritated or inflamed anorectal areas

Warnings

For external use only

When using this product

- do not exceed recommended dosage unless recommended by a physician
- do not put this product into rectum by using fingers or any mechanical device or applicator

Stop use and ask doctor if

- condition worsens or does not improve within 7 days
- bleeding occurs

Keep out of reach of children. If swallowed, get medical help or contact Poison Control Center right away.

Directions

- adults: when practical, cleanse the affected area with mild soap & warm water and rinse thoroughly
- gently dry by blotting with toilet tissue or soft cloth before application
- pump once onto toilet paper & if desired, fold to deflate foam. Apply to affected area by patting then flush.
- postpartum, add foam on top of each maxi pad for healing relief.
- use up to 6 times daily or after each bowel movement
- children under 12 years of age: consult a doctor

Other information

- pack foam in hospital bag for instant relief post-delivery and place in bathroom for at home recovery.
- store at room temperature or in fridge for extra cooling.

Inactive ingredients

aloe barbadensis leaf juice, coco glucoside, glycerin, lactic acid, propanediol, purified water, sodium benzoate

QUESTIONS OR COMMENTS?

TNDickinsons.com
1•888•860•2279

Dist. by: Dickinson Brands Inc.
East Hampton, CT 06424

PRINCIPAL DISPLAY PANEL - 147 mL Bottle Label

#1 PHYSICIAN RECOMMENDED*
WITCH HAZEL BRAND

T.N.
DICKINSON'S®

Witch
hazel®

NEW
Medicated Cooling Foam

HEMORRHOIDAL RELIEF

Immediately Soothes
Inflamed, burning, itching
Hemorrhoidal, Vaginal &
Postpartum Perineal areas

MADE WITH
100% NATURAL
WITCH HAZEL

HEMORRHOIDAL WIPE ALTERNATIVE

5 FL. OZ. (147 mL) = Approx. 185 Wipes or Pads

Learn More!